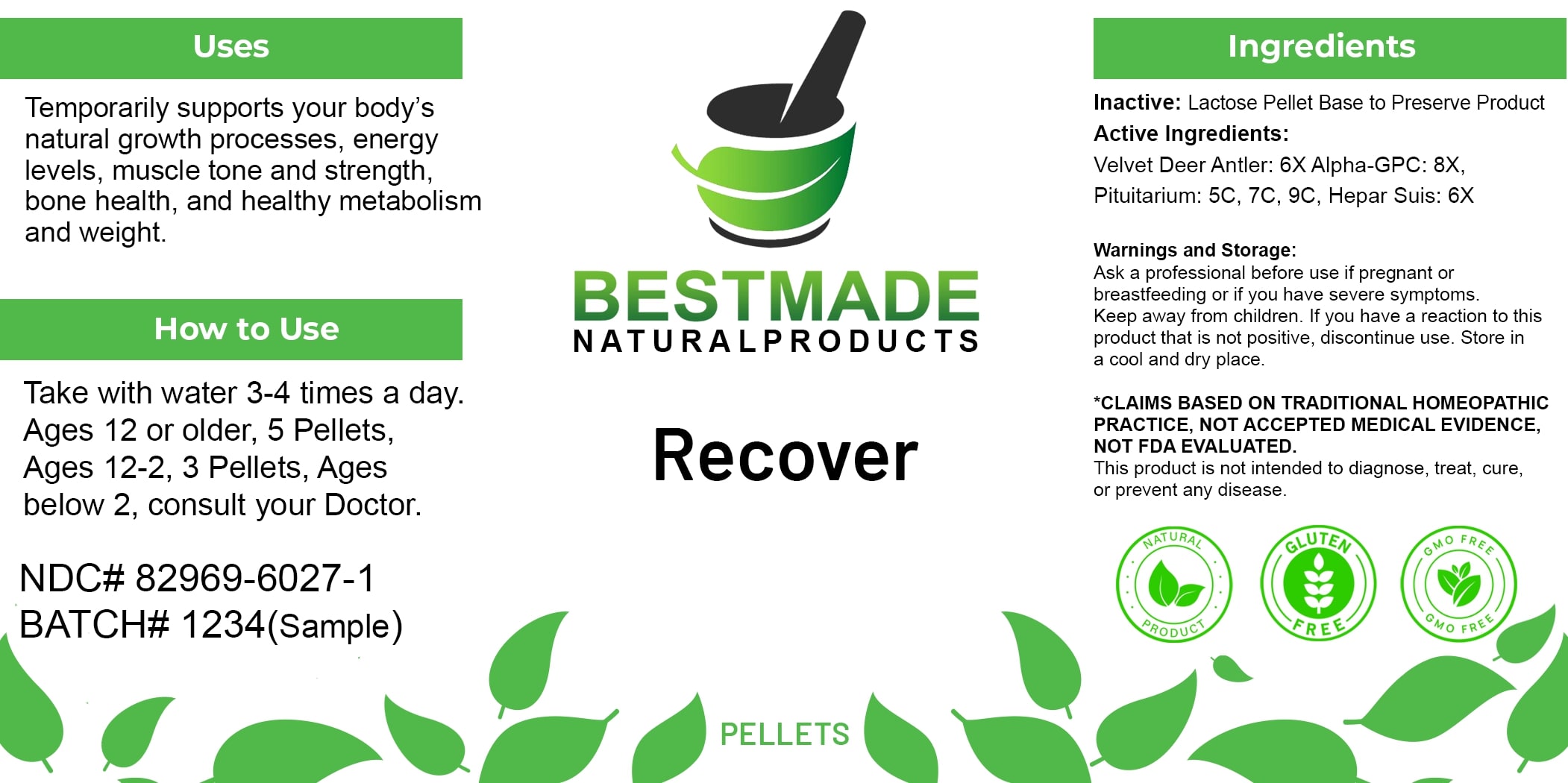 DRUG LABEL: Bestmade Natural Products Recover
NDC: 82969-6027 | Form: TABLET, SOLUBLE
Manufacturer: Bestmade Natural Products
Category: homeopathic | Type: HUMAN OTC DRUG LABEL
Date: 20250314

ACTIVE INGREDIENTS: CERVUS ELAPHUS VELVET 6 [hp_X]/6 [hp_X]; GLYCEROPHOSPHOCHOLINE 6 [hp_X]/6 [hp_X]; PORK LIVER 6 [hp_X]/6 [hp_X]; SUS SCROFA PITUITARY GLAND, POSTERIOR 6 [hp_X]/6 [hp_X]
INACTIVE INGREDIENTS: LACTOSE 6 [hp_X]/6 [hp_X]

Recover

Inactive: Lactose Pellet Base to Preserve Remedy

DOSAGE AND ADMINISTRATION

How to Use

Take with water 3-4 times a day. Ages 12 or older, 5 Pellets, Ages 12-2, 3 Pellets, Ages below 2, consult your Doctor.

Active Ingredients:
Velvet Deer Antler: 6X, Alpha-GPC: 8X, Pituitarium: 5C, 7C, 9C, Hepar Suis: 6X

Uses

Temporarily supports your body's natural growth processes, energy levels, muscle tone and strength, bone health, and healthy metabolism and weight.

*CLAIMS BASED ON TRADITIONAL HOMEOPATHIC PRACTICE, NOT ACCEPTED MEDICAL EVIDENCE, NOT FDA EVALUATED.

This product is not intended to diagnose, treat, cure, or prevent any disease.

Uses

Temporarily supports your body's natural growth processes, energy levels, muscle tone and strength, bone health, and healthy metabolism and weight.

*CLAIMS BASED ON TRADITIONAL HOMEOPATHIC PRACTICE, NOT ACCEPTED MEDICAL EVIDENCE, NOT FDA EVALUATED.

This product is not intended to diagnose, treat, cure, or prevent any disease.

KEEP OUT OF REACH OF CHILDREN

Warnings and Storage:

Ask a professional before use if pregnant or breastfeeding or if you have severe symptoms. Keep away from children. If you have a reaction to this product that is not positive, discontinue use. Store in a cool and dry place.

Warnings and Storage:

Ask a professional before use if pregnant or breastfeeding or if you have severe symptoms. Keep away from children. If you have a reaction to this product that is not positive, discontinue use. Store in a cool and dry place.

*CLAIMS BASED ON TRADITIONAL HOMEOPATHIC PRACTICE, NOT ACCEPTED MEDICAL EVIDENCE NOT FDA EVALUATED.
This product is not intended to diagnose, treat, cure, or prevent any disease.

Entire package label